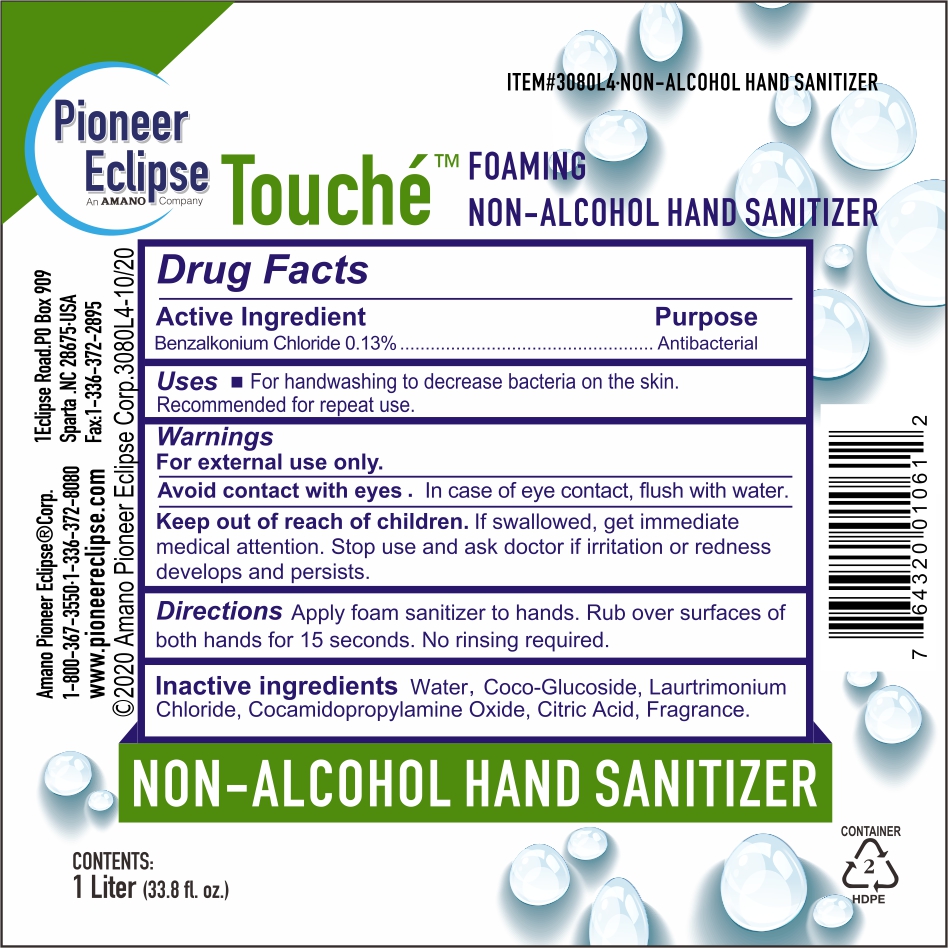 DRUG LABEL: Foaming Non Alcohol Hand Sanitizer
NDC: 80401-111 | Form: LIQUID
Manufacturer: Uweport LLC
Category: otc | Type: HUMAN OTC DRUG LABEL
Date: 20211230

ACTIVE INGREDIENTS: BENZALKONIUM CHLORIDE 0.13 g/100 mL
INACTIVE INGREDIENTS: COCAMIDOPROPYLAMINE OXIDE 0.3 mL/100 mL; LAURTRIMONIUM CHLORIDE 0.3 mL/100 mL; COCO GLUCOSIDE 1.5 mL/100 mL; WATER; CHLOROCITRIC ACID 0.02 mL/100 mL

The hand sanitizer is manufactured using only the following United States Pharmacopoeia (USP) grade ingredients in the preparation of the product (percentage in final product formulation) consistent with World Health Organization (WHO) recommendations:

1. Benzalkonium Chloride (0.13% w/v).
2. Coco-Glucoside (1.5% v/v).
3. Laurtrimonium Chloride (0.3% v/v).
4. Cocamidopropylamine Oxide (0.3% v/v).
5. Citric Acid (0.02% v/v).
6. Sterile distilled water or boiled cold water.

The firm does not add other active or inactive ingredients. Different or additional ingredients may impact the quality and potency of the product.

Active Ingredient(s)

Benzalkonium Chloride 0.13% w/v. Purpose: Antiseptic

Purpose

Antiseptic, Hand Sanitizer

Use

Hand Sanitizer to help reduce bacteria that potentially can cause disease. For use when soap and water are not available.

Warnings

For external use only. Flammable. Keep away from heat or flame

Do not use

- in children less than 2 months of age
- on open skin wounds

When using this product keep out of eyes, ears, and mouth. In case of contact with eyes, rinse eyes thoroughly with water.
Stop use and ask a doctor if irritation or rash occurs. These may be signs of a serious condition.
Keep out of reach of children. If swallowed, get medical help or contact a Poison Control Center right away.

Stop use and ask a doctor if irritation or rash occurs. These may be signs of a serious condition.

Keep out of reach of children. If swallowed, get medical help or contact a Poison Control Center right away.

Directions

- Place enough product on hands to cover all surfaces. Rub hands together until dry.
- Supervise children under 6 years of age when using this product to avoid swallowing.

Other information

- Store between 15-30C (59-86F)
- Avoid freezing and excessive heat above 40C (104F)

Inactive ingredients

Coco-Glucoside, Laurtrimonium Chloride, Cocamidopropylamine Oxide, Citric Acid, purified water USP

Package Label - Principal Display Panel

1000 ml NDC: 80401-102-10